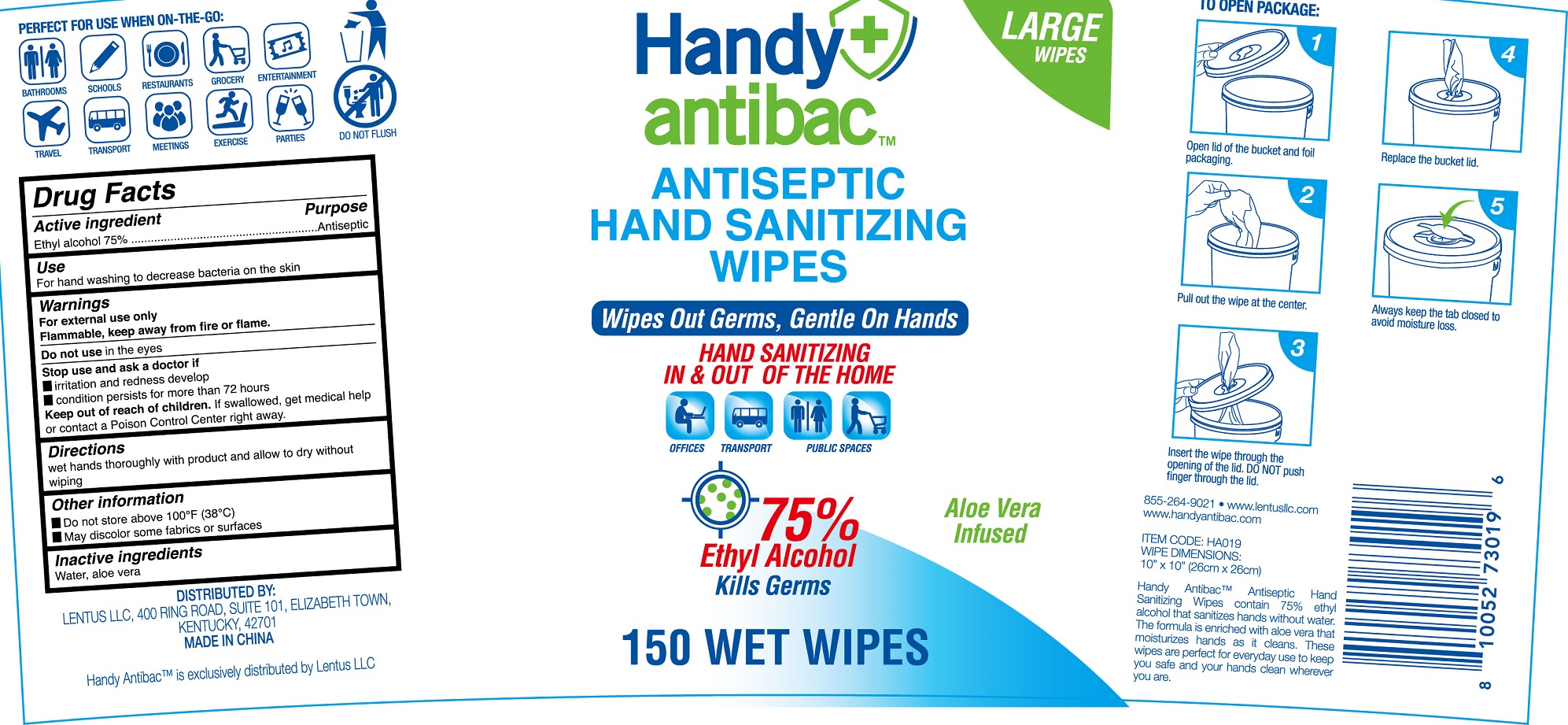 DRUG LABEL: Handy antibac Antiseptic Hand Sanitizing Wipes
NDC: 77435-101 | Form: CLOTH
Manufacturer: HAINING LILY CLEANING PRODUCTS CO., LTD
Category: otc | Type: HUMAN OTC DRUG LABEL
Date: 20200813

ACTIVE INGREDIENTS: ALCOHOL 75 g/100 g
INACTIVE INGREDIENTS: WATER

Antiseptic Wipes

Active Ingredient

Ethyl Alcohol 75%

Purpose

Antiseptic

USE

For hand washing to decrease bacteria on the skin.

Warning

- Flammable, keep away from fire or flame. For external use only.
- When using this product, Do not use in or near the eyes. In case of contact, rinse eyes thoroughly with water.

- Stop use and ask a doctor, if irritaion and redness develop; condition persists for ore than 72 hours

Other Information：

- Do not store above 100℉ (38 ℃)
- May discolor some fabrics or surface

KEEP OUT OF REACH OF CHILDREN

●If swallowed, get medical help or contact a Poison Contrl Center right away.

Directions

- Wet hands thoroughluy with produt and allow to dry without wiping

Inactive ingredients

Water, aloe vera